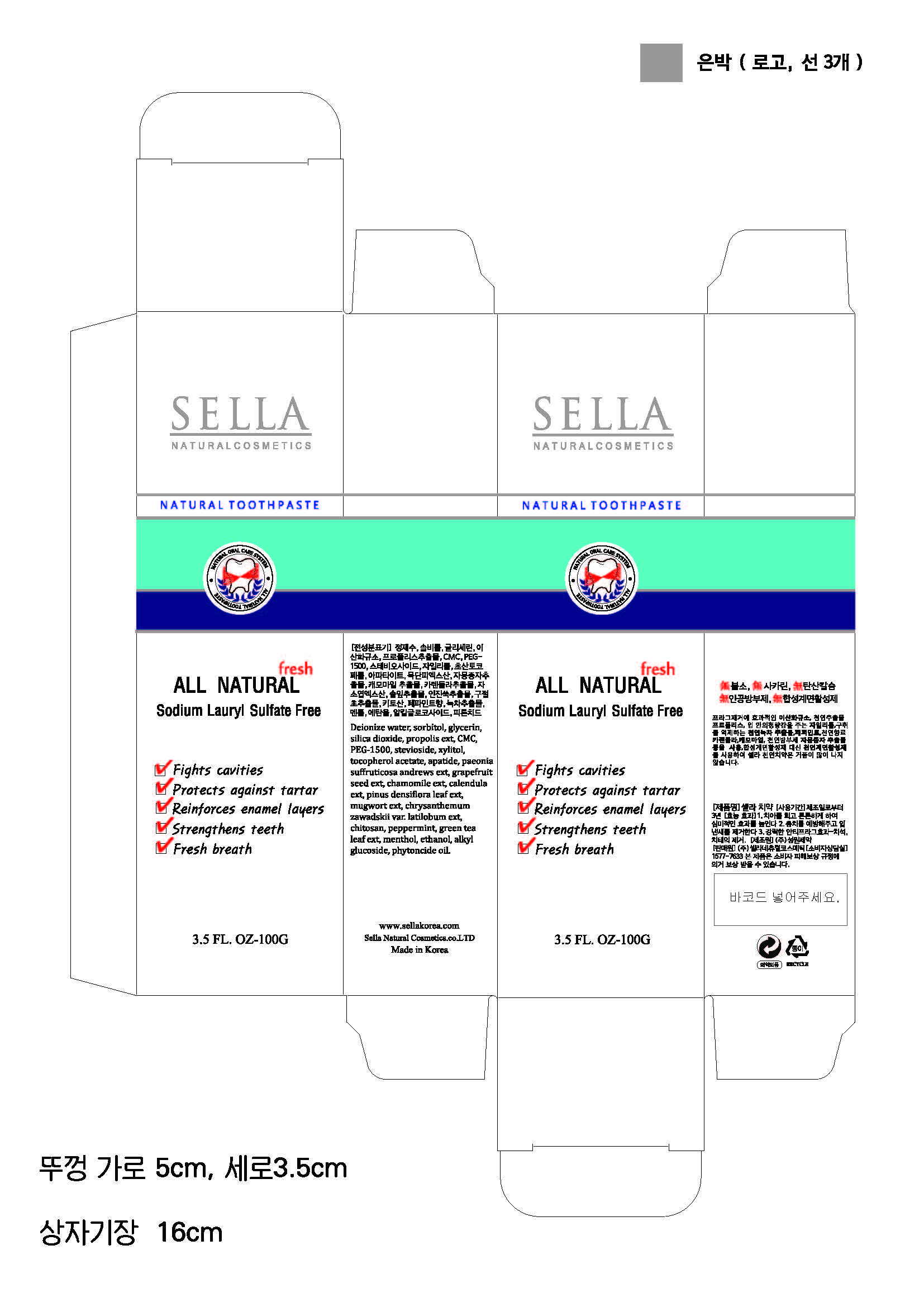 DRUG LABEL: SELLA NATURAL
NDC: 69603-1401 | Form: PASTE, DENTIFRICE
Manufacturer: Sella Natural Cosmetics Co.,Ltd.
Category: otc | Type: HUMAN OTC DRUG LABEL
Date: 20150211

ACTIVE INGREDIENTS: MENTHOL 0.2 g/100 g
INACTIVE INGREDIENTS: GLYCERIN; ALCOHOL

Drug Facts

ACTIVE INGREDIENT

MENTHOL

INACTIVE INGREDIENT

sorbitol, glycerin, stevioside, xylitol, alcohol, etc

PURPOSE

skin protectant

keep out of reach of the children

INDICATIONS AND USAGE

apply toothpaste on soft bristle toothbrush
brush thoroughly after each meal

WARNINGS

if irritation occurs discontinue use

DOSAGE AND ADMINISTRATION

for oral use only